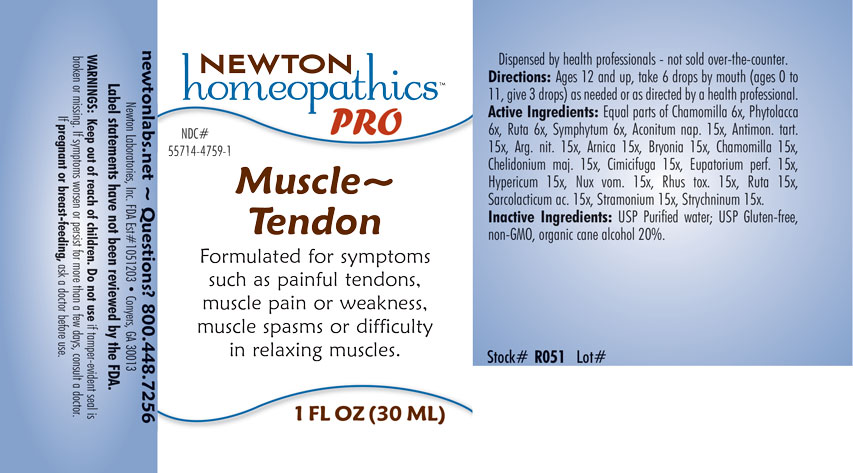 DRUG LABEL: Muscle-Tendon
NDC: 55714-4759 | Form: LIQUID
Manufacturer: Newton Laboratories, Inc.
Category: homeopathic | Type: HUMAN OTC DRUG LABEL
Date: 20201204

ACTIVE INGREDIENTS: ACONITUM NAPELLUS 15 [hp_X]/1 mL; ANTIMONY POTASSIUM TARTRATE 15 [hp_X]/1 mL; SILVER NITRATE 15 [hp_X]/1 mL; ARNICA MONTANA 15 [hp_X]/1 mL; BRYONIA ALBA ROOT 15 [hp_X]/1 mL; MATRICARIA CHAMOMILLA 15 [hp_X]/1 mL; CHELIDONIUM MAJUS 15 [hp_X]/1 mL; BLACK COHOSH 15 [hp_X]/1 mL; EUPATORIUM PERFOLIATUM FLOWERING TOP 15 [hp_X]/1 mL; HYPERICUM PERFORATUM 15 [hp_X]/1 mL; STRYCHNOS NUX-VOMICA SEED 15 [hp_X]/1 mL; TOXICODENDRON PUBESCENS LEAF 15 [hp_X]/1 mL; RUTA GRAVEOLENS FLOWERING TOP 15 [hp_X]/1 mL; LACTIC ACID, L- 15 [hp_X]/1 mL; DATURA STRAMONIUM 15 [hp_X]/1 mL; STRYCHNINE 15 [hp_X]/1 mL; PHYTOLACCA AMERICANA ROOT 6 [hp_X]/1 mL; COMFREY ROOT 6 [hp_X]/1 mL
INACTIVE INGREDIENTS: WATER; ALCOHOL

Muscle 4759L

INDICATIONS & USAGE SECTION

Formulated for symptoms such as painful tendons, muscle pain or weakness, muscle spasms or difficulty in relaxing muscles.

DOSAGE & ADMINISTRATION SECTION

Directions: Ages 12 and up, take 6 drops by mouth (ages 0 to 11, give 3 drops) as needed or as directed by a health professional.

OTC - ACTIVE INGREDIENT SECTION

Equal parts of Chamomilla 6x, Phytolacca 6x, Ruta 6x, Symphytum 6x Aconitum nap. 15x, Antimon. tart. 15x, Arg. nit. 15x, Arnica 15x, Bryonia 15x, Chamomilla 15x, Chelidonium majus 15x, Cimicifuga 15x, Eupatorium perf. 15x, Hypericum 15x, Nux vom. 15x, Rhus toxicodendron 15x, Ruta 15x,Sarcolacticum ac. 15x, Stramonium 15x, Strychninum 15x. .

OTC - PURPOSE SECTION

Formulated for symptoms such as painful tendons, muscle pain or weakness, muscle spasms or difficulty in relaxing muscles.

INACTIVE INGREDIENT SECTION

Inactive Ingredients: USP Purified Water; USP Gluten-free, non-GMO, organic cane alcohol 20%.

QUESTIONS SECTION

newtonlabs.net – Questions? 800.448.7256

Newton Laboratories, Inc. FDA Est # 1051203 - Conyers, GA 30013

WARNINGS SECTION

WARNINGS: Keep out of reach of children. Do not use if tamper-evident seal is broken or missing. If symptoms worsen or persist for more than a few days, consult a doctor. If pregnant or breast-feeding, ask a doctor before use

OTC - PREGNANCY OR BREAST FEEDING SECTION

. If pregnant or breast-feeding, ask a doctor before use

OTC - KEEP OUT OF REACH OF CHILDREN SECTION

Keep out of reach of children